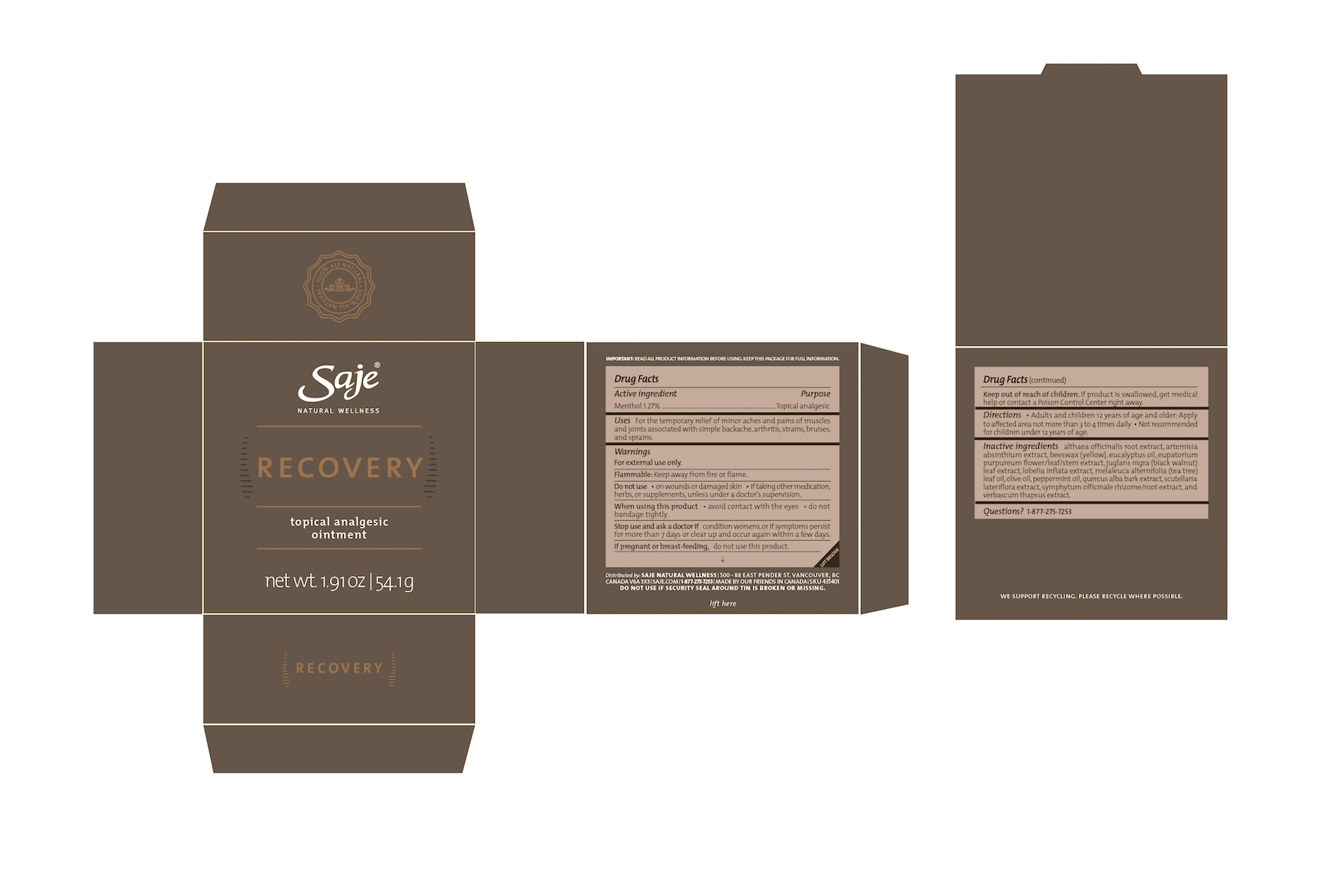 DRUG LABEL: Recovery
NDC: 70983-008 | Form: OINTMENT
Manufacturer: Saje Natural Business Inc.
Category: otc | Type: HUMAN OTC DRUG LABEL
Date: 20160929

ACTIVE INGREDIENTS: MENTHOL 12.7 mg/1 g
INACTIVE INGREDIENTS: ALTHAEA OFFICINALIS ROOT; WORMWOOD; YELLOW WAX; EUCALYPTUS OIL; EUTROCHIUM PURPUREUM FLOWERING TOP; JUGLANS NIGRA LEAF; LOBELIA INFLATA; TEA TREE OIL; OLIVE OIL; PEPPERMINT OIL; QUERCUS ALBA BARK; SCUTELLARIA LATERIFLORA; COMFREY ROOT; VERBASCUM THAPSUS

Recovery Topical Analgesic Ointment (54.1 g)

IMPORTANT: READ ALL PRODUCT INFORMATION BEFORE USING. KEEP THIS PACKAGE FOR FULL INFORMATION.

DRUG FACTS Active Ingredient

Menthol 1.27%

Purpose Topical Analgesic

Uses For the temporary relief of minor aches and pains of muscles and joints associated with simple backache, arthritis, strains, bruises and sprains.

Warnings

For external use only.

Flammable: Keep away from fire or flame.

Do not use

- on wounds or damaged skin
- if taking other medication, herbs, or supplements, unless under a doctor's supervision

When using this product

- avoid contact with the eyes
- do not bandage tightly

Stop use and ask a doctor if

condition worsens, or if symptoms persist for more than 7 days or clear up and occur again within a few days.

If pregnant or breast-feeding,

do not use this product.

Keep out of reach of children.

If product is swallowed, get medical help or contact a Poison Control Center right away.

Directions

- Adults and children 12 years of age and older: Apply to affected area

DOSAGE AND ADMINISTRATION

not more than 3 to 4 times daily.

- Not recommended for children under 12 years of age.

Inactive ingredients

Althaea officinalis root extract, artemisia absinthium extract, beeswax (yellow), eucalyptus oil, eupatorium purpureum flower/leaf/stem extract, juglans nigra (black walnut) leaf extract, lobelia inflata extract, melaleuca alternifolia (tea tree) leaf oil, olive oil, peppermint oil, quercus alba bark extract, scutellaria lateriflora extract, symphytum officinale rhizome/root extract, and verbascum thapsus extract.

Questions?

1-877-275-7253

Distributed by: SAJE NATURAL WELLNESS 500-88 E. Pender St. Vancouver, BC Canada V6A 3X3 | saje.com | 1-877-275-7253 | Made by our friends in Canada

DO NOT USE IF SECURITY SEAL AROUND TIN IS BROKEN OR MISSING.

SKU 435401

Lift Here

We support recycling. Please recycle where possible.

Recovery Topical Analgesic Ointment 54.1 g

Saje® Natural Wellness

Recovery

Topical Analgesic Ointment

net wt. 1.91 oz | 54.1 g